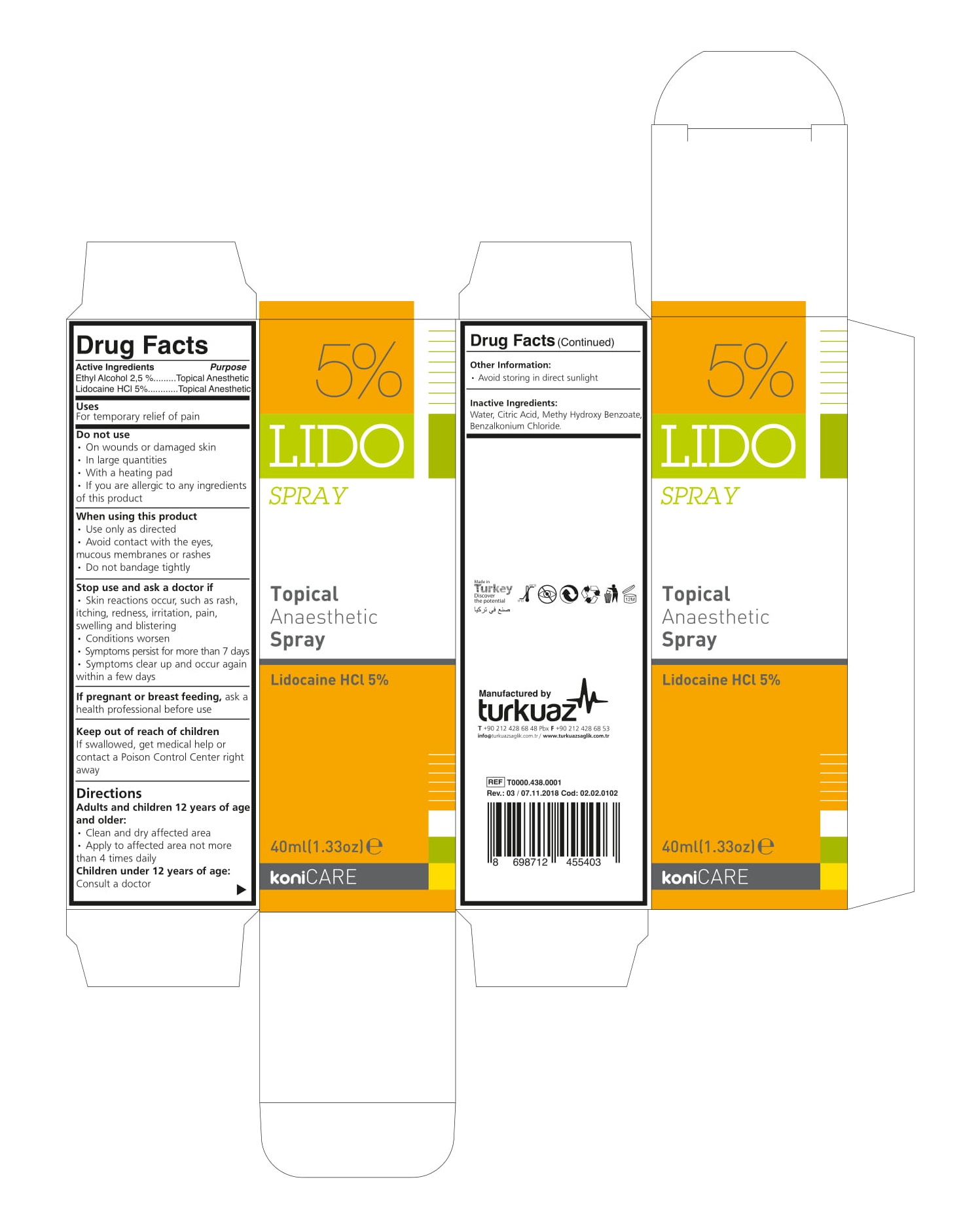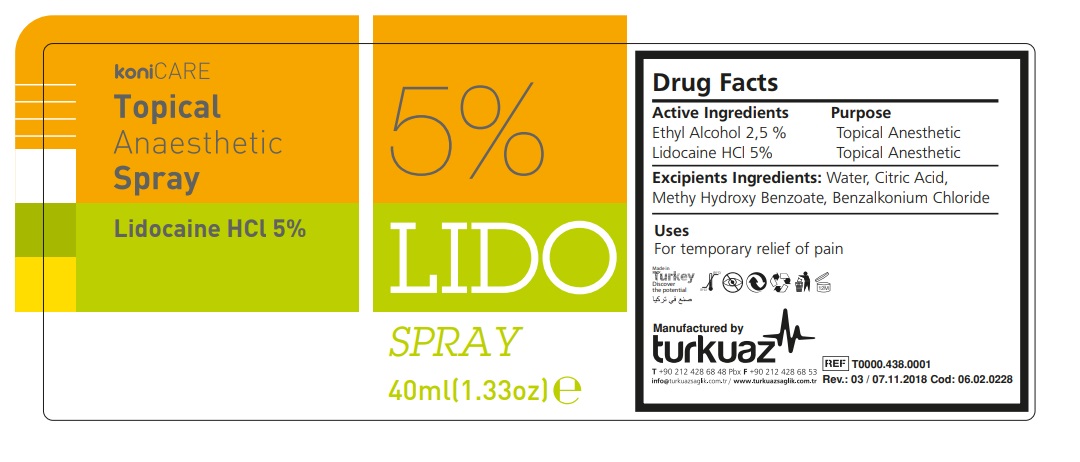 DRUG LABEL: KONICARE 5%
NDC: 73107-902 | Form: SPRAY
Manufacturer: Turkuaz Saglik Hizmetleri Medikal Temizlik KImyasal Urunler Sanayi ve Tic. AS
Category: otc | Type: HUMAN OTC DRUG LABEL
Date: 20220712

ACTIVE INGREDIENTS: LIDOCAINE HYDROCHLORIDE 5 g/100 mL; ALCOHOL 2.5 mL/100 mL
INACTIVE INGREDIENTS: WATER; CITRIC ACID ACETATE; BENZALKONIUM CHLORIDE; METHYLPARABEN

KoniCare 5% Lido Spray

Active Ingredients

- Ethyl Alcohol 2,5 %.........Topical Anesthetic
- Lidocaine HCl 5%............Topical Anesthetic

INDICATIONS AND USAGE

Uses:

For temporary relief of pain

WARNINGS

Do not use

• On wounds or damaged skin

• In large quantities

• With a heating pad

• If you are allergic to any ingredients of this product

Stop use and ask a doctor if,

• Use only as directed

• Avoid contact with the eyes, mucous membranes or rashes

• Do not bandage tightly

Stop use and ask a doctor if,

• Skin reactions occur, such as rash, itching, redness, irritation, pain, swelling and blistering

• Conditions worsen

• Symptoms persist for more than 7 days

• Symptoms clear up and occur again within a few days

If pregnant or breast feeding,

If swallowed, get medical help or contact a Poison Control Center right away

Keep out of reach of children

If swallowed, get medical help or contact a Poison Control Center right away

Directions

Adults and children 12 years of age and older:

- Clean and dry affected area
- Apply to affected area not more than 4 times daily

Children under 12 years of age:

- Consult a doctor

Inactive Ingredients:

Water, Citric Acid, Methy Hydroxy Benzoate, Benzalkonium Chloride.

Konicare 5% LidoSpray

Ethyl Alcohol 2.5 % Topical Anesthetic
Lidocaine HCl 5% Topical Anesthetic